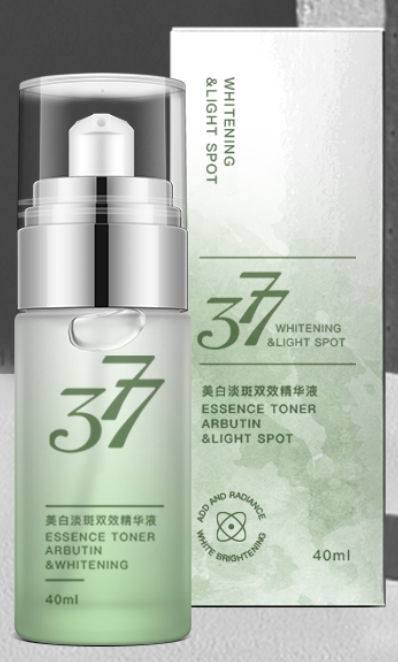 DRUG LABEL: Whitening serum
NDC: 84507-015 | Form: LIQUID
Manufacturer: Guangdong Miaolian Cosmetics Co., Ltd.
Category: otc | Type: HUMAN OTC DRUG LABEL
Date: 20240819

ACTIVE INGREDIENTS: 3-O-ETHYL ASCORBIC ACID 0.4 mg/100 mL
INACTIVE INGREDIENTS: WATER

DOSAGE AND ADMINISTRATION

Triple action
-Moisturizer
-Dark spots remover
-Brightens skin

Warning.
1.Before use, perform a skin test on your arm and discontinue use if you have allergy symptoms or skin abnormalities.
2、For external use only, avoid contact with eyes when used
3、Keep out of reach of children

INACTIVE INGREDIENT

water..

INDICATIONS AND USAGE

Removes and fades out stubborn dark spots, acne scars,sun spots and blemishes. It helps restore a clearer and more radiant even-toned complexion while also smoothing out dry skin.

Keep out of reach of children

PURPOSE

For facial whitening